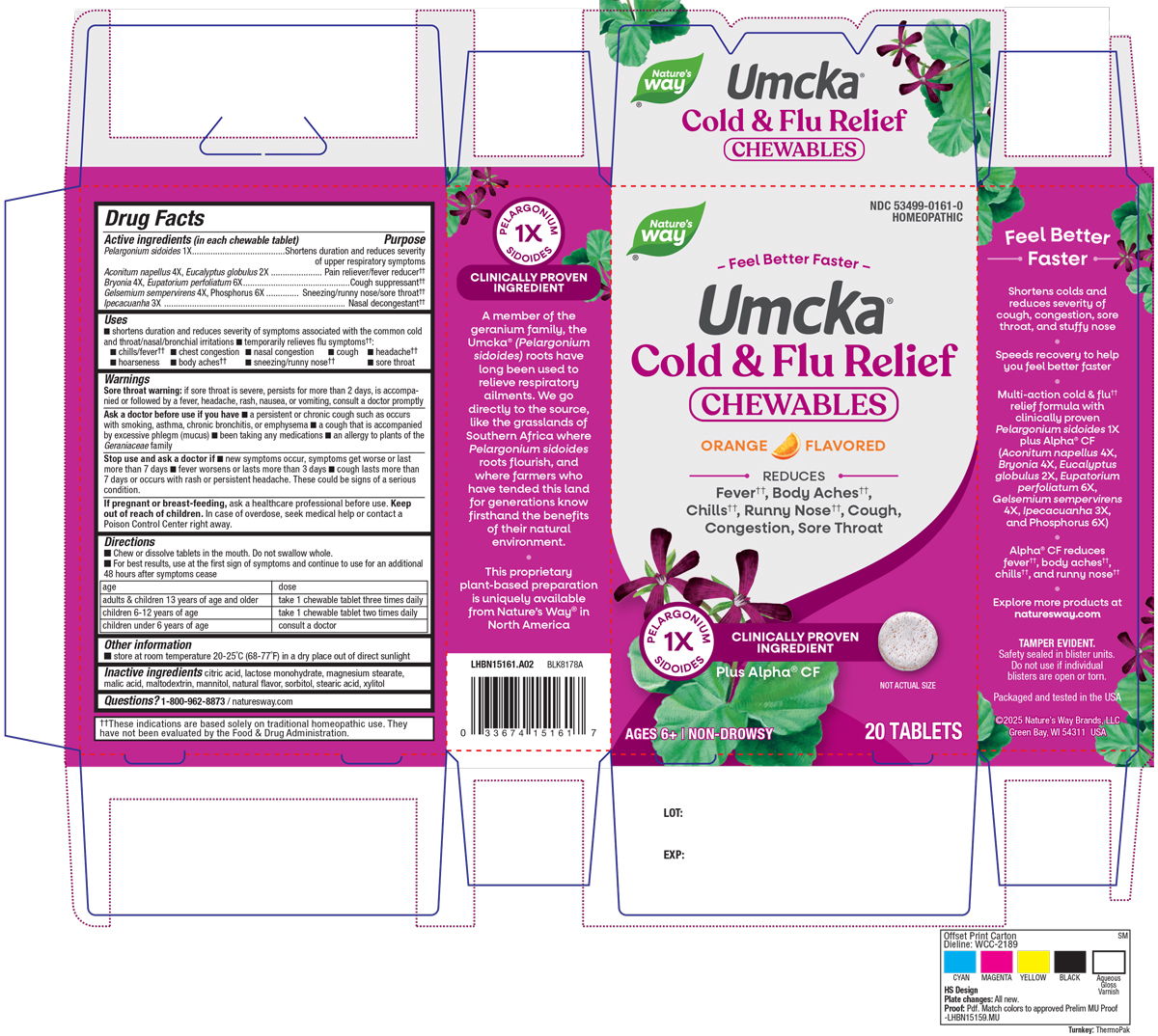 DRUG LABEL: Cold Flu Relief Orange
NDC: 53499-0161 | Form: TABLET, CHEWABLE
Manufacturer: Schwabe North America, Inc.
Category: homeopathic | Type: HUMAN OTC DRUG LABEL
Date: 20250825

ACTIVE INGREDIENTS: PELARGONIUM SIDOIDES ROOT 1 [hp_X]/1 1; ACONITUM NAPELLUS 4 [hp_X]/1 1; BRYONIA ALBA ROOT 4 [hp_X]/1 1; EUCALYPTUS GLOBULUS LEAF 2 [hp_X]/1 1; EUPATORIUM PERFOLIATUM FLOWERING TOP 6 [hp_X]/1 1; GELSEMIUM SEMPERVIRENS ROOT 4 [hp_X]/1 1; IPECAC 3 [hp_X]/1 1; PHOSPHORUS 6 [hp_X]/1 1
INACTIVE INGREDIENTS: CITRIC ACID MONOHYDRATE; LACTOSE MONOHYDRATE; MAGNESIUM STEARATE; MALIC ACID; MALTODEXTRIN; MANNITOL; SORBITOL; STEARIC ACID; XYLITOL

Cold + Flu Relief Orange Chewables

Active Ingredients

Pelargonium sidoides 1X

Aconitum napellus 4X

Eucalyptus globulus 2X

Bryonia 4X

Eupatorium perfoliatum 6X

Gelsemium sempervirens 4X

Phosphorus 6X

Ipecacuanha 3X

Inactive Ingredients

Citric Acid

Lactose Monohydrate

Magnesium Stearate

Malic Acid

Maltodextrin

Mannitol

Natural Flavor

Sorbitol

Stearic Acid

Xylitol

Dosage & Administration

Directions:

Chew or dissolve tablets in the mouth. Do not swallow whole.

For best results, use at first sign of symptoms and continue to use for an additional 48 hours after symptoms cease.
Adults & children 13 years of age and older: Take 1 chewable tablet three times daily.
Children 6-12 years of age: Take 1 chewable tablet two times daily.
Children under 6 years of age: Consult a doctor.

Indications & Usage

Shortens duration and reduces severity of symptoms associated with the common cold and throat/nasal/bronchial irritations, and temporarily relieves flu symptoms: chills/fever, chest congestion, nasal congestion, cough, headache, hoarseness, body aches, sneezing/runny nose, sore throat.

Purpose

Shortens duration and reduces severity of symptoms associated with the common cold and throat/nasal/bronchial irritations, and temporarily relieves flu symptoms: chills/fever, chest congestion, nasal congestion, cough, headache, hoarseness, body aches, sneezing/runny nose, sore throat.

Warnings

Sore throat warning: if sore throat is severe, persists for more than 2 days, is accompanied or followed by a fever, headache, rash, nausea, or vomiting, consult a doctor promptly.

Ask Doctor

Ask a doctor before use if you have a persistent or chronic cough such as occurs with smoking, asthma, chronic bronchitis, or emphysema, a cough accompanied by excessive phlegm (mucus), been taking any medications, an allergy to plants of the Geraniaceae family.

Stop use

Stop use and ask a doctor if new symptoms occur, symptoms get worse or last more than 7 days, fever worsens or lasts more than 3 days, cough lasts more than 7 days or occurs with rash or persistent headache.

These could be signs of a serious condition.

Pregnancy or Breast Feeding

If pregnant or breast-feeding, ask a healthcare professional before use.

Keep out of reach of children

Overdose

In case of overdoese, seek medical help or contact a Poison Control Center right away.